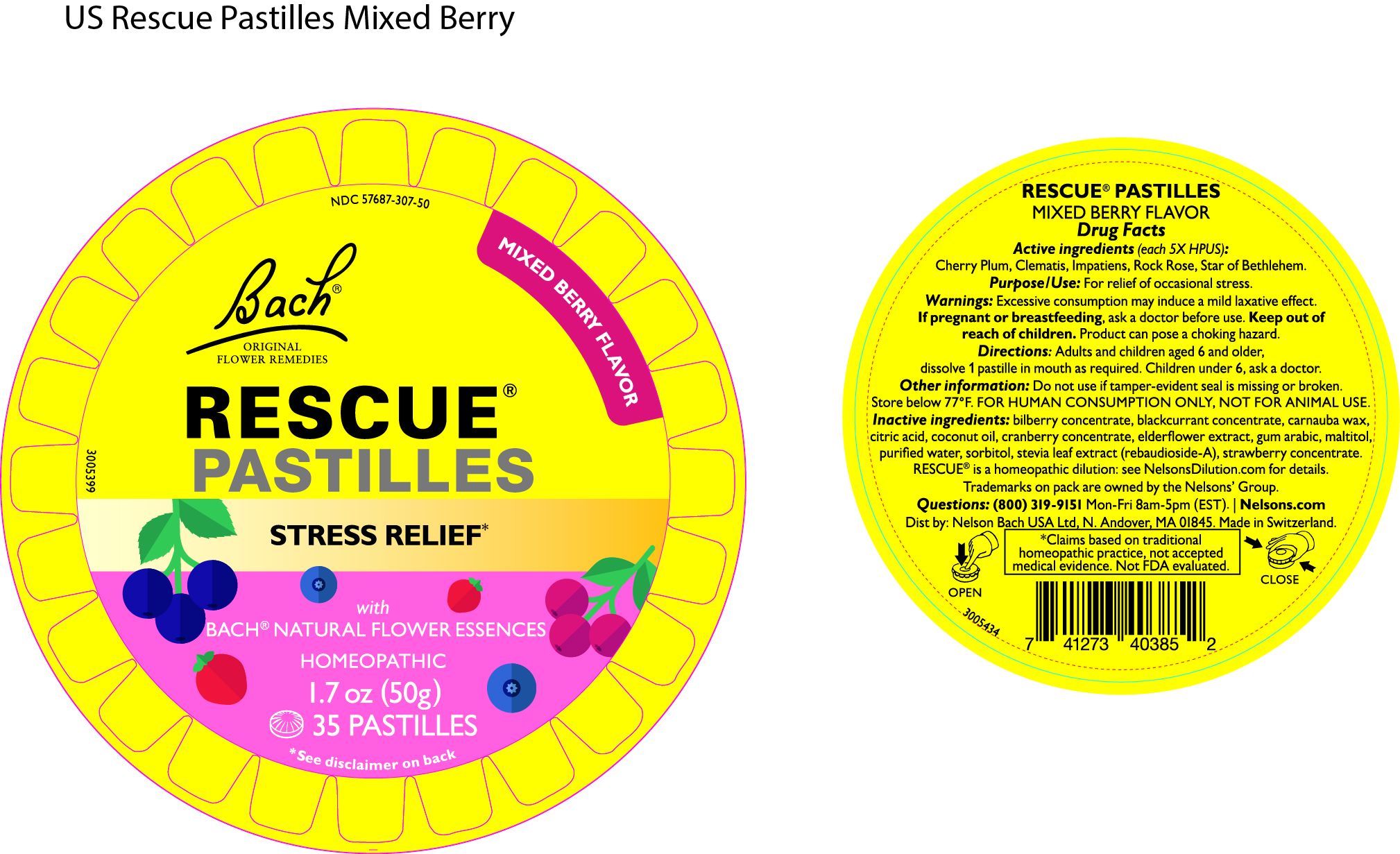 DRUG LABEL: Rescue Pastilles Mixed Berry Flavour
NDC: 57687-307 | Form: LOZENGE
Manufacturer: Nelson Bach USA Limited
Category: homeopathic | Type: HUMAN OTC DRUG LABEL
Date: 20240808

ACTIVE INGREDIENTS: HELIANTHEMUM NUMMULARIUM FLOWER 5 [hp_X]/1 1; ORNITHOGALUM UMBELLATUM FLOWERING TOP 5 [hp_X]/1 1; IMPATIENS GLANDULIFERA FLOWER 5 [hp_X]/1 1; PRUNUS CERASIFERA FLOWER 5 [hp_X]/1 1; CLEMATIS VITALBA FLOWER 5 [hp_X]/1 1
INACTIVE INGREDIENTS: SORBITOL SOLUTION 70%; BLACK CURRANT; SAMBUCUS NIGRA FLOWER; STRAWBERRY; CITRIC ACID MONOHYDRATE; BILBERRY; CRANBERRY; ACACIA; MALTITOL; WATER; STEVIOL; COCONUT OIL; CARNAUBA WAX

Rescue Pastilles MIxed Berry Flavour

Uses

For the relief of occasional stress

Directions

Adults and children aged 6 and older, dissolve 1 pastilles in the mouth as required. Children under 6, ask a doctor.

Active Ingredients (Each 5x HPUS)

Cherry Plum, Clematis, Impatiens, Rock Rose, Star of Bethlehem.

Inactive Ingredients

bilberry concentrate, blackcurrant concentrate, carnauba wax, citric acid, coconut oil, cranberry concentrate, elderflower extract, gum arabic, maltitol, purified water, sorbitol, stevia leaf extract (rebaudioside-A), strawberry concentrate.

Warnings

Excessive consumption may induce a mild laxative effect. If pregnant or breastfeeding, ask a doctor before use. Keep out of reach of children. Product can pose a choking hazard.

Other Information

Do not use if tamper-evident seal is missing or broken. Store below 77o F. For human consumption only, not for animal use.

Questions?

(800) 319-9151 Mon-Fri 8am-5pm (EST)

Distributed by

Nelson Bach USA Ltd, N Andover, MA 01845

OTC Purpose

For Releif of occassional stress

Keep out of reach of children. Product can pose a choking hazard.

Principal Display Panel - 50g Pastille Container

NDC 57687-307-50

Mixed Berry Flavour

Bach Original Flower Remedies

Rescue Pastilles

Stress Relief*

With Bach Natural Flower Essences

Homeopathic

1.7oz (50g)

35 Pastilles

*see disclaimer on back